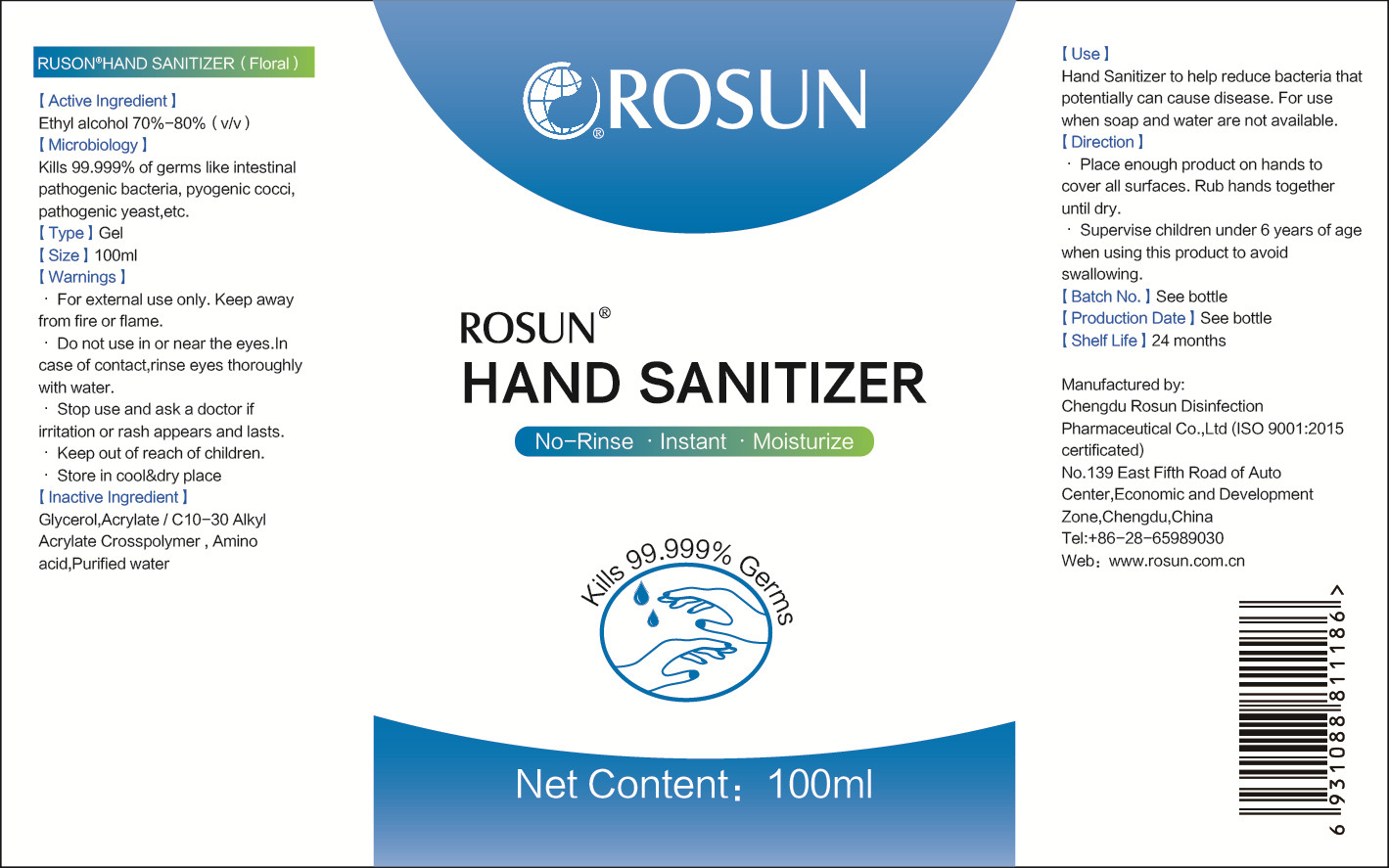 DRUG LABEL: Hand Sanitizer
NDC: 54586-001 | Form: GEL
Manufacturer: Chengdu Rosun Disinfection Pharmaceutical Co., Ltd.
Category: otc | Type: HUMAN OTC DRUG LABEL
Date: 20200518

ACTIVE INGREDIENTS: ALCOHOL 75 mL/100 mL
INACTIVE INGREDIENTS: GLYCERIN; AMINO ACIDS, ESSENTIAL; CARBOMER INTERPOLYMER TYPE A (ALLYL SUCROSE CROSSLINKED); WATER

DOSAGE AND ADMINISTRATION

Store in cool&dry place

INACTIVE INGREDIENT

Acrylate / C10-30 Alkyl Acrylate Crosspolymer

Glycerol

Amino acid

Purified Water

INDICATIONS AND USAGE

Place enough product on hands to cover all surfaces. Rub hands together until dry.

ACTIVE INGREDIENT

Ethyl Alcoho

keep out of reach of children

PURPOSE

Disinfection
Sterilization
No Rinseing

WARNINGS

1.For external use only. Keep away from fire or flame.
2.Do not use in or near the eyes.In case of contact,rinse eyes thoroughly with water.
3.Stop use and ask a doctor if iritation or rash appears and lasts.
4.Keep out of reach of children.

5.Store in cool&dry place